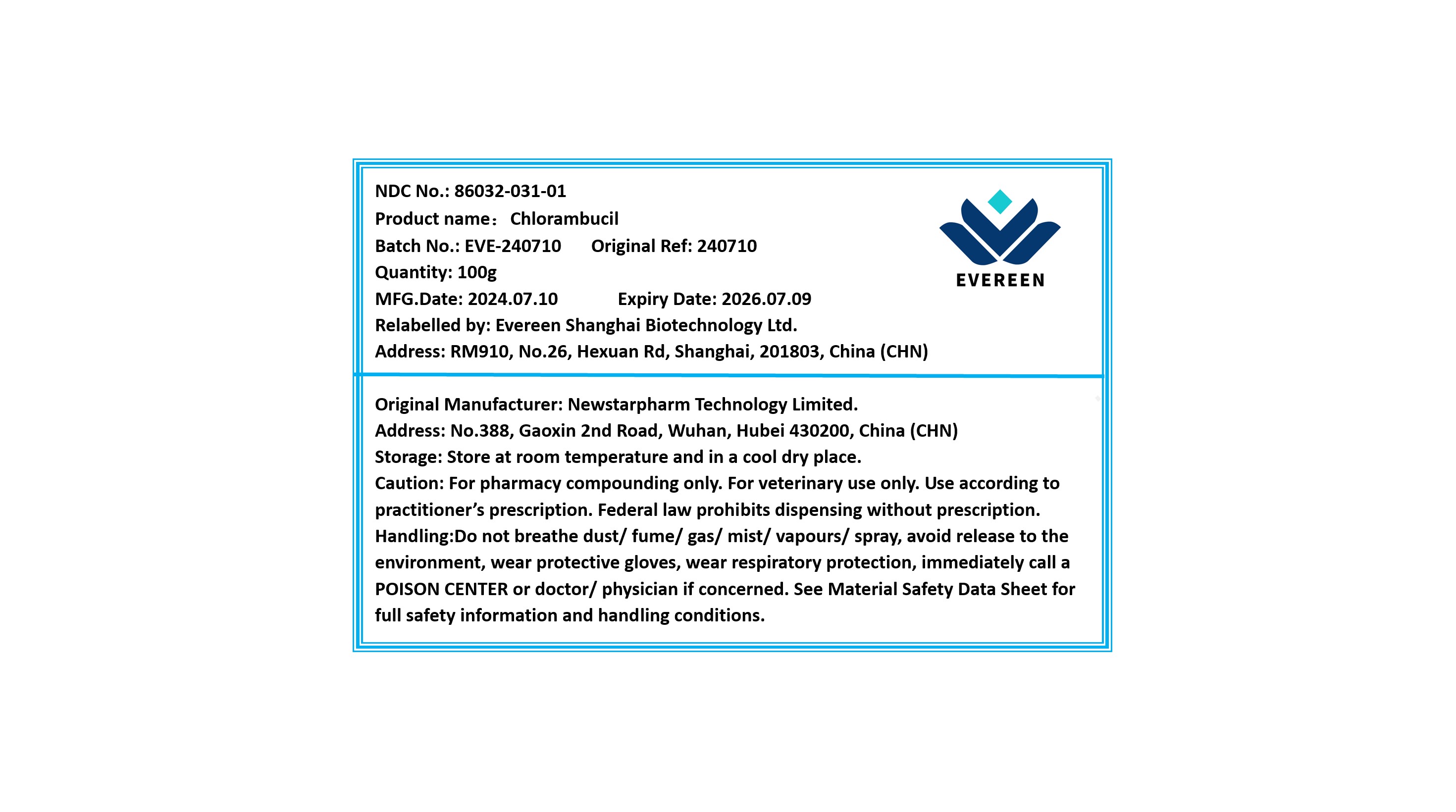 DRUG LABEL: Chlorambucil
NDC: 86032-031 | Form: POWDER
Manufacturer: Evereen Shanghai Biotechnology Ltd.
Category: other | Type: BULK INGREDIENT - ANIMAL DRUG
Date: 20241125

ACTIVE INGREDIENTS: CHLORAMBUCIL 1 g/1 g

Chlorambucil